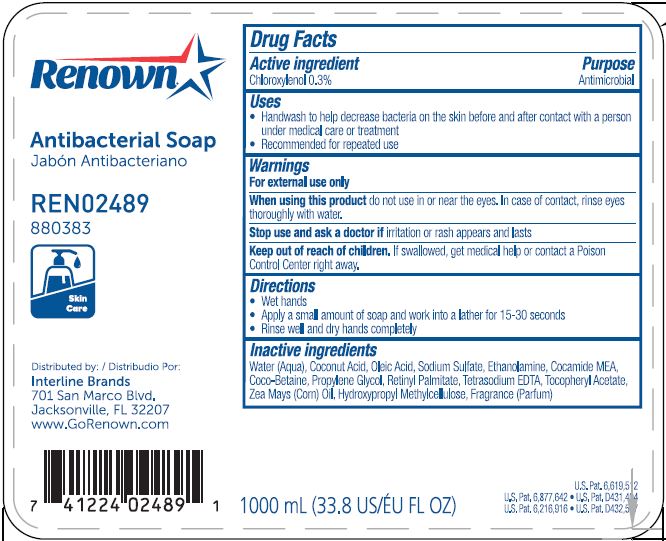 DRUG LABEL: RENOWN Antimicrobial So ap
NDC: 71896-051 | Form: LIQUID
Manufacturer: Interline Brands, Inc.
Category: otc | Type: HUMAN OTC DRUG LABEL
Date: 20241220

ACTIVE INGREDIENTS: CHLOROXYLENOL 0.003 mg/1 mL
INACTIVE INGREDIENTS: WATER; COCONUT ACID; OLEIC ACID; SODIUM SULFATE; MONOETHANOLAMINE; COCO MONOETHANOLAMIDE; COCO-BETAINE; PROPYLENE GLYCOL; VITAMIN A PALMITATE; EDETATE SODIUM; .ALPHA.-TOCOPHEROL ACETATE; CORN OIL; HYPROMELLOSE, UNSPECIFIED

RENOWN® Antimicrobial Soap

Active ingredient

Chloroxylenol 0.3%

Purpose

Antimicrobial

Use

• Handwash to help decrease bacteria on the skin

• Recommended for repeated use

Warnings

For external use only

When using this product do not use in or near the eyes. In case of contact, rinse eyes thoroughly with water.

Stop use and ask a doctor ifirritation or rash appears and lasts

Keep out of reach of children.If swallowed, get medical help or contact a Poison Control Center right away.

Directions

• Wet hands

• Apply a small amount of product and work into a lather

• Rinse well and dry hands completely

Inactive ingredients

Water (Aqua), Coconut Acid, Oleic Acid, Sodium Sulfate, Ethanolamine, Cocamide MEA, Coco-Betaine, Propylene Glycol, Retinyl Palmitate, Tetrasodium EDTA, Tocopheryl Acetate, Zea Mays (Corn) Oil, Hydroxypropyl Methylcellulose, Fragrance (Parfum)